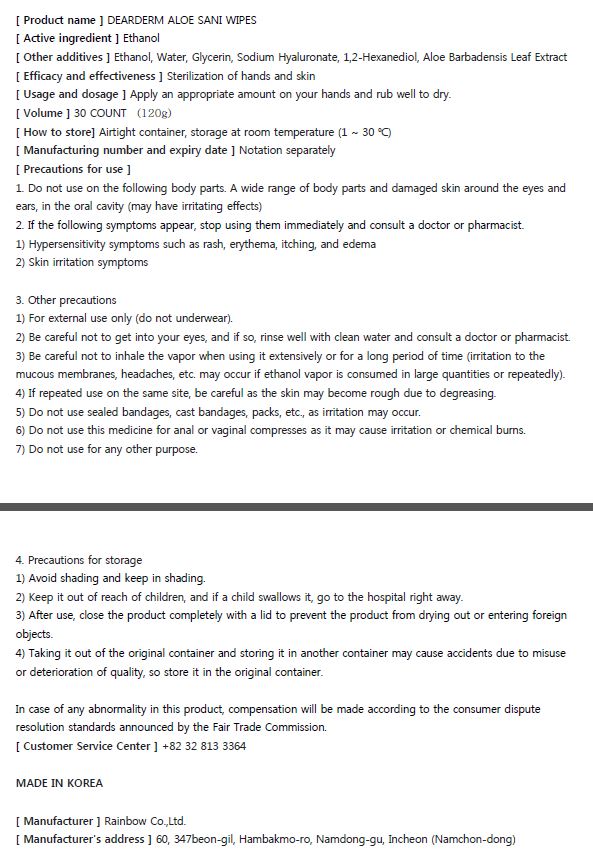 DRUG LABEL: Dearderm ALOE SANI WIPES
NDC: 74247-0013 | Form: GEL
Manufacturer: Rainbow Co Ltd
Category: otc | Type: HUMAN OTC DRUG LABEL
Date: 20200610

ACTIVE INGREDIENTS: ALCOHOL 70 mL/100 g
INACTIVE INGREDIENTS: GLYCERIN; HYALURONATE SODIUM; ALOE VERA LEAF; 1,2-HEXANEDIOL; WATER

Drug Facts

ACTIVE INGREDIENT

alcohol

INACTIVE INGREDIENT

Ethanol, Water, Glycerin, Sodium Hyaluronate, 1,2-Hexanediol, Aloe Barbadensis Leaf Extract

PURPOSE

Sterilization of hands and skin

KEEP OUT OF REACH OF THE CHILDREN

INDICATIONS AND USAGE

Apply to clean, dry hands. Apply sufficient amount to thoroughly wet all surfaces of hands and fingers. Rub onto hands until dry.

Supervise children in the use of this product.

WARNINGS

■ Flammable. Keep away from fire or flame.

■ For external use only.

■ Do not use in eyes.

■ lf swallowed, get medical help promptly.

■ Stop use, ask doctor lf irritation occurs.

■ Keep out of reach of children.

DOSAGE AND ADMINISTRATION

for external use only